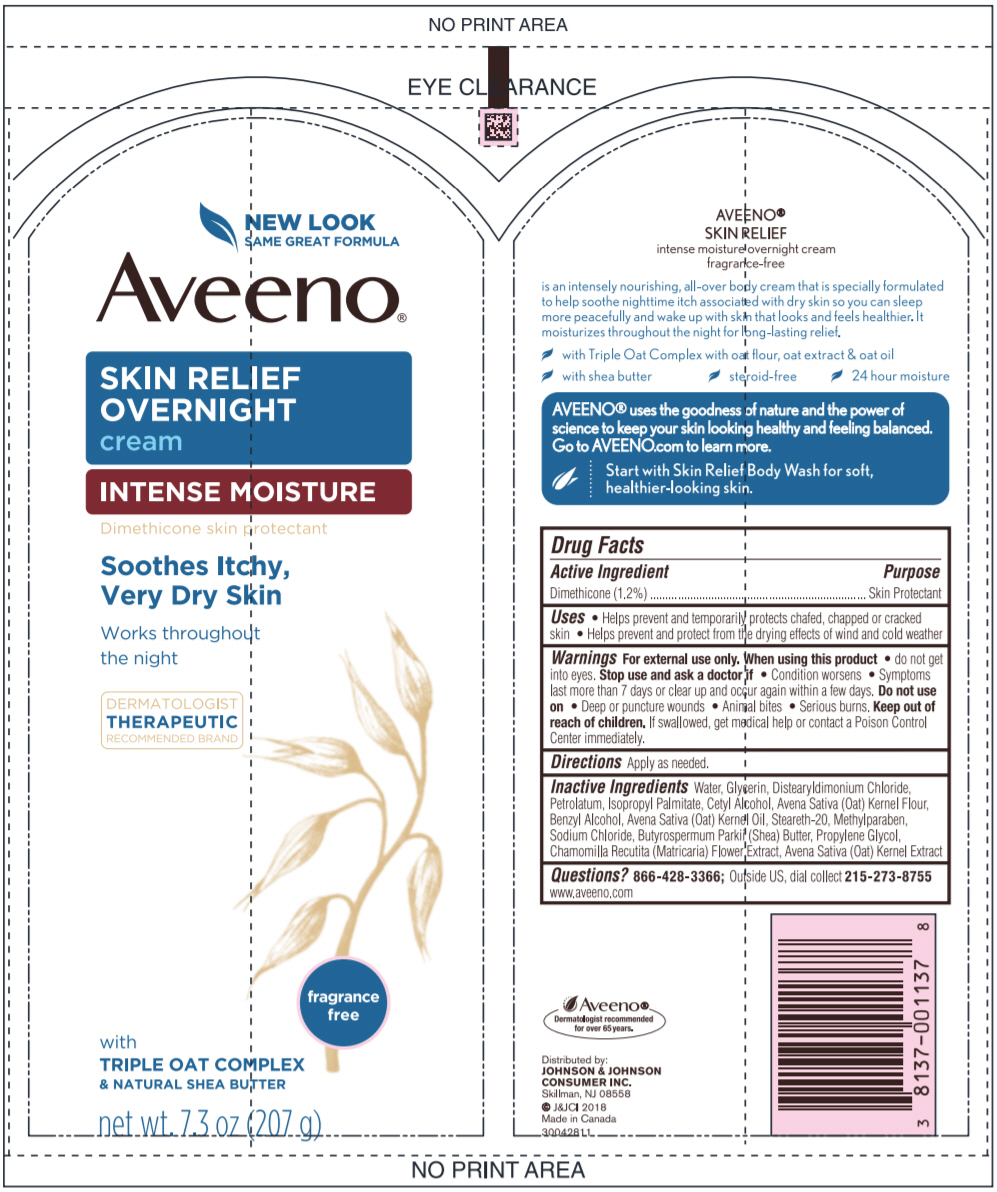 DRUG LABEL: Aveeno Skin Relief Overnight
NDC: 69968-0488 | Form: CREAM
Manufacturer: Kenvue Brands LLC
Category: otc | Type: HUMAN OTC DRUG LABEL
Date: 20241105

ACTIVE INGREDIENTS: DIMETHICONE 12 mg/1 g
INACTIVE INGREDIENTS: WATER; GLYCERIN; DISTEARYLDIMONIUM CHLORIDE; PETROLATUM; ISOPROPYL PALMITATE; CETYL ALCOHOL; OATMEAL; BENZYL ALCOHOL; OAT KERNEL OIL; STEARETH-20; METHYLPARABEN; OAT; SODIUM CHLORIDE; SHEA BUTTER; PROPYLENE GLYCOL; MATRICARIA CHAMOMILLA

Aveeno SKIN RELIEF OVERNIGHT cream

Drug Facts

Active ingredient

Dimethicone 1.2 %

Purpose

Skin Protectant

Uses

- Helps prevent and temporarily protects chafed, chapped, or cracked skin
- Helps prevent and protect from the drying effects of wind and cold weather

Warnings

For external use only.

When using this product

do not get into eyes.

Stop use and ask a doctor if

condition worsens

- symptoms last more than 7 days or clear up and occur again within a few days.

Do not use on

Deep or puncture wounds

- Animal bites
- Serious burns.

Keep out of reach of children. If swallowed, get medical help or contact a Poison Control Center immediately.

Directions

Apply as needed.

Other information

Store at Room Temperature

Inactive ingredients

water, glycerin, distearyldimonium chloride, petrolatum, isopropyl palmitate, cetyl alcohol, avena sativa (oat) kernel flour, benzyl alcohol, avena sativa (oat) kernel oil, steareth-20, methylparaben, sodium chloride, butyrospermum parkii (shea) butter, propylene glycol, chamomilla recutita (matricaria) flower extract, avena sativa (oat) kernel extract

Questions?

Call toll-free 866-428-3366 or 215-273-8755 (collect) or visit www.aveeno.com

Distributed by:
JOHNSON & JOHNSON
CONSUMER INC.
Skillman, NJ 08558

PRINCIPAL DISPLAY PANEL - 207 g Tube Label

NEW LOOK
SAME GREAT FORMULA
Aveeno®
SKIN RELIEF
OVERNIGHT
cream
INTENSE MOISTURE
Dimethicone skin protectant
Soothes Itchy,
Very Dry Skin
Works throughout
the night
DERMATOLOGIST
THERAPEUTIC
RECOMMENDED BRAND

fragrance
free

with
TRIPLE OAT COMPLEX
& NATURAL SHEA BUTTER
net wt. 7.3 oz (207 g)